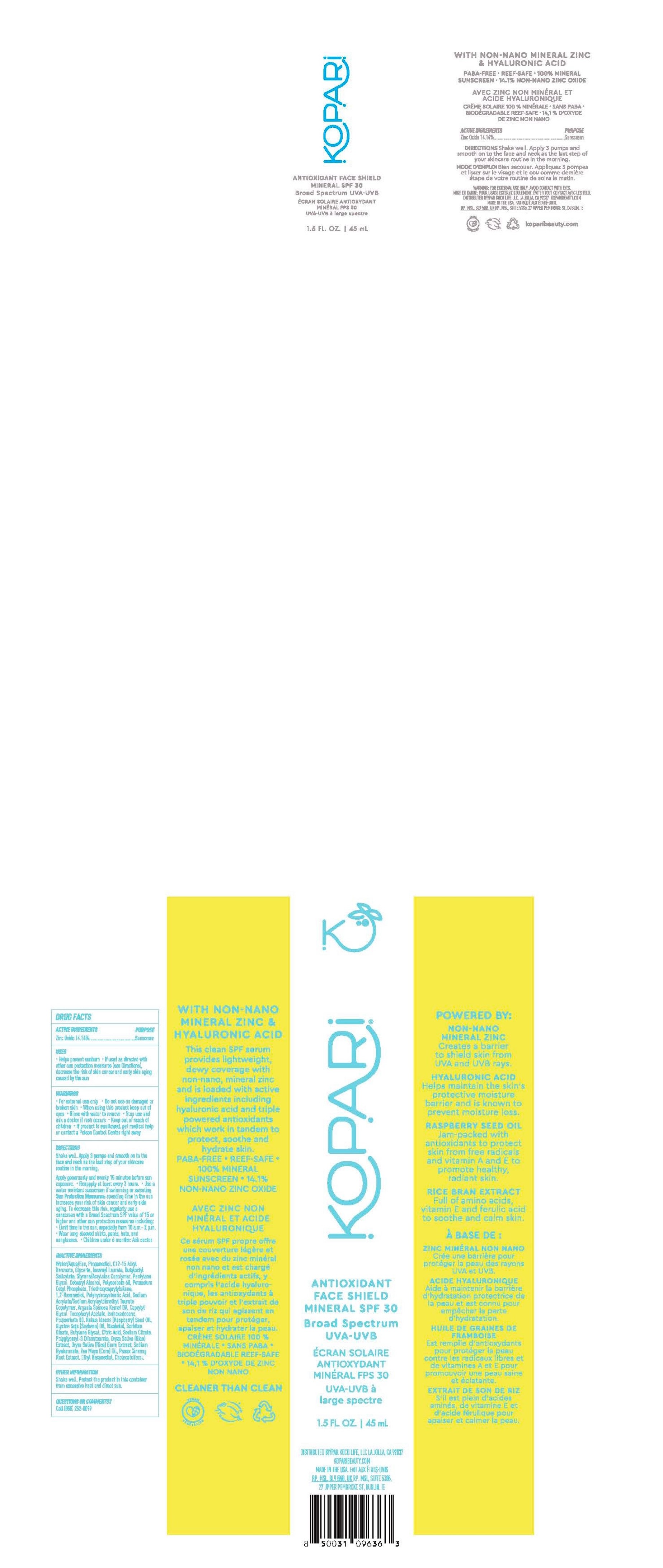 DRUG LABEL: Antioxidant Face Shield Mineral SPF30
NDC: 84130-007 | Form: CREAM
Manufacturer: Koco Life LLC
Category: otc | Type: HUMAN OTC DRUG LABEL
Date: 20240628

ACTIVE INGREDIENTS: ZINC OXIDE 141.4 mg/1 mL
INACTIVE INGREDIENTS: STYRENE/ACRYLAMIDE COPOLYMER (500000 MW); SODIUM CITRATE; RICE GERM; ASIAN GINSENG; ETHOHEXADIOL; SODIUM ACRYLATE/SODIUM ACRYLOYLDIMETHYLTAURATE COPOLYMER (4000000 MW); SOYBEAN OIL; BUTYLENE GLYCOL; ISOAMYL LAURATE; TRIETHOXYCAPRYLYLSILANE; CORN OIL; CITRIC ACID MONOHYDRATE; PROPANEDIOL; CAPRYLYL GLYCOL; POLYSORBATE 80; CETOSTEARYL ALCOHOL; POLYGLYCERYL-3 DIISOSTEARATE; BUTYLOCTYL SALICYLATE; GLYCERIN; PENTYLENE GLYCOL; POLYSORBATE 60; ARGAN OIL; ISOHEXADECANE; LEVOMENOL; CHOLECALCIFEROL; POTASSIUM CETYL PHOSPHATE; SORBITAN MONOOLEATE; HYALURONATE SODIUM; ALKYL (C12-15) BENZOATE; WATER; .ALPHA.-TOCOPHEROL ACETATE; RASPBERRY SEED OIL; 1,2-HEXANEDIOL; POLYHYDROXYSTEARIC ACID (2300 MW)

Antioxidant Face Shield Mineral SPF30

Active ingredients

Zinc Oxide 14.14%

Purpose

Zinc Oxide 14.14%............Sunscreen

Uses

• Helps prevent sunburn

• If used as directed with othersun protection measures (see Directions), decrease therisk of skin cancer and early skin aging caused by the sun

Warnings

• For external use only

• Do not use on damaged or broken skin

• When using this product keep out of eyes

• Rinse with water to remove

• Stop use and ask a doctor if rash occurs

• Keep out of reach of children

• If product is swallowed, get medical help or contact aPoison Control Center right away

Directions

Shake well. Apply 3 pumps and smooth on to the face and neck as the last step of your skincare routine in the morning.

Apply generously and evenly 15 minutes before sun exposure. • Reappply at least every 2 hours. • Use a water resistant sunscreen if swimming or sweating

Sun Protection Measures: spending time in the sun increases your risk of skin cancer and early skin aging. To decrease this risk, regularly use a sunscreen with a Broad Spectrum SPF value of 15 or higher and other sun protection measures including:• Limit time in the sun, especially from 10 a.m.- 2 p.m. • Wear long-sleeved shirts, pants, hats, and sunglasses. • Children under 6 months: Ask doctor

Inactive ingredients

Water/Aqua/Eau, Propanediol, C12-15 Alkyl Benzoate, Glycerin, lsoamyl Laurate, Butyloctyl Salicylate, Styrene/Acrylates Copolymer, Pentylene Glycol, Cetearyl Alcohol, Polysorbate 60, Potassium Cetyl Phosphate, Triethoxycaprylylsilane, 1,2-Hexanediol, Polyhydroxystearic Acid, Sodium Acrylate/Sodium Acryloyldimethyl Taurate Copolymer, Argania Spinosa Kernel Oil, Caprylyl Glycol, Tocopheryl Acetate, lsohexadecane, Polysorbate 80, Rubus ldaeus (Raspberry) Seed Oil, Glycine Soja (Soybean) Oil, Bisabolol, Sorbitan Oleate, Butylene Glycol, Citric Acid, Sodium Citrate. Polyglyceryl-3 Diisostearate, Oryza Saliva (Rice) Extract, Oryza Saliva (Rice) Germ Extract, Sodium Hyaluronate, Zea Mays (Corn) Oil, Panax Ginseng Root Extract, Ethyl Hexanediol, Cholecalciferol.

Other information

Shake well. Protect the product in this container from excessive heat and direct sun.

Questions or comments?

Call (858) 252-0099

PACKAGE LABEL

Kopari

Antioxidant

Face Shield

Mineral SPF 30

Broad Spectrum

UVA-UVB

1.5 FL. OZ. | 45 mL